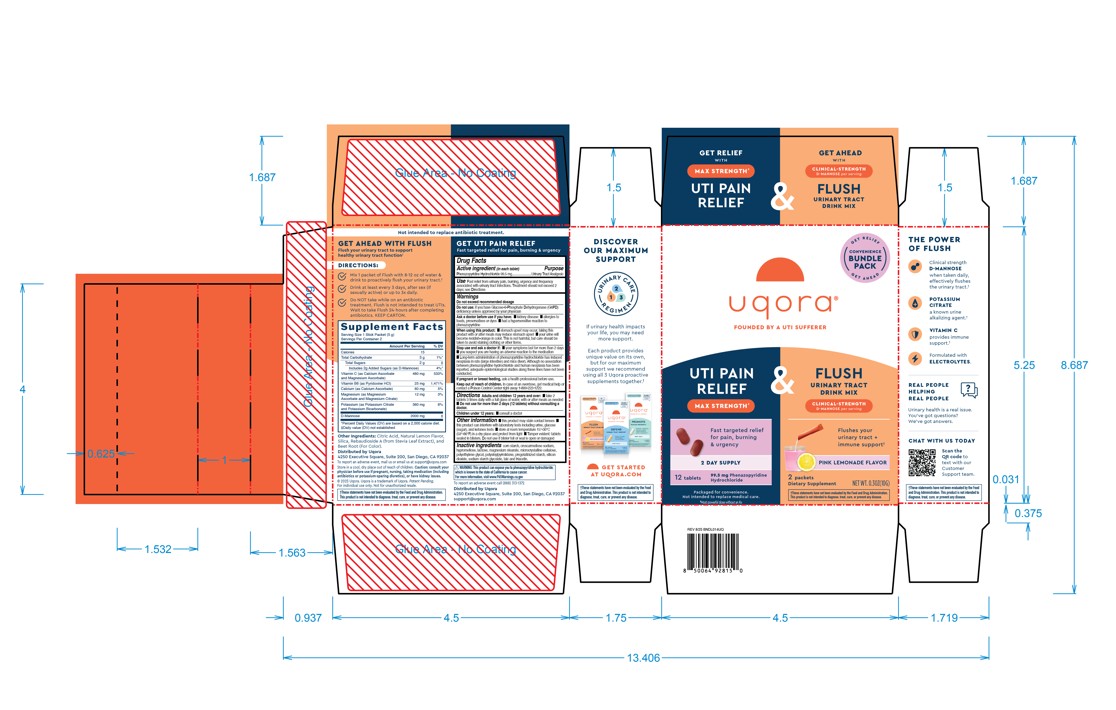 DRUG LABEL: Uqora Maximum UTI Pain Relief and Flush Convenience Bundle
NDC: 73712-600 | Form: KIT | Route: ORAL
Manufacturer: Bonafide Health, LLC dba Uqora
Category: otc | Type: HUMAN OTC DRUG LABEL
Date: 20251110

ACTIVE INGREDIENTS: PHENAZOPYRIDINE HYDROCHLORIDE 99.5 mg/1 1
INACTIVE INGREDIENTS: POLYETHYLENE GLYCOL, UNSPECIFIED; HYPROMELLOSES; MAGNESIUM STEARATE; SILICON DIOXIDE; SODIUM STARCH GLYCOLATE TYPE A; CROSCARMELLOSE SODIUM; LACTOSE, UNSPECIFIED FORM; POVIDONE, UNSPECIFIED; TALC; TRIACETIN; STARCH, CORN; CELLULOSE, MICROCRYSTALLINE

Uqora Maximum UTI Pain Relief + Flush Convenience Bundle

Uqora Maximum UTI Pain Relief

Drug Facts

Active ingredient (in each tablet)

Phenazopyridine Hydrochloride 99.5 mg

Purpose

Active ingredient (in each tablet) | Purpose
Phenazopyridine Hydrochloride 99.5mg | Urinary Tract Analgesic

Use

Fast relief from urinary pain, burning, urgency and frequency associated with urinary tract infections. Treatment should not exceed 2 days; see Directions.

Warnings

Do not exceed recommended dosage

Do Not Use

- If you have Glucose-6-Phosphate Dehydrogenase (G6PD) deficiency unless approved by your physician

Ask a doctor before use if you have:

- kidney disease
- allergies to foods, preservatives or dyes
- had a hypersensitive reaction to phenazopyridine

When Using This Product

- stomach upset may occur, taking this product with or after meals may reduce stomach upset
- your urine will become reddish-orange in color. This is not harmful, but care should be taken to avoid staining clothing or other items.

Stop use and ask a doctor if:

- your symptoms last for more than 2 days
- you suspect you are having an adverse reaction to the medication

Long-term administration of phenazopyridine hydrochloride has induced neoplasia in rats (large intestine) and mice (liver). Although
no association between phenazopyridine hydrochloride and human neoplasia has been reported, adequate epidemiological studies along these lines have not been conducted.

If pregnant or breast feeding, ask a health professional before use.

Keep out of the reach of children.In case of overdose, get medical help or contact a Poison Control Center right away 1-800-222-1222

Directions

Adults and children 12 years and over:

take 2 tablets 3 times daily with a full glass of water, with or after meals as needed
Do not use for more than 2 days (12 tablets) without consulting a doctor.

Children under 12 years:consult a doctor

Other Information

- this product may stain contact lenses
- this product can interfere with laboratory tests including urine, glucose (sugar), and ketones tests
- store at room temperature 15°-30°C (59°-86°F) in a dry place and protect from light
- Tamper evident: tablets sealed in blisters. Do not use if blister foil or seal is open or damaged

Inactive ingredients

corn starch, croscarmellose sodium, hypromellose, lactose, magnesium stearate, microcrystalline cellulose, polyethylene glycol, polyvinylpyrrolidone, pregelatinized starch, silicon dioxide, sodium starch glycolate, talc and triacetin.

Additional Items

FLUSH Urinary Tract Drink Mix

2 packets

Dietary Supplement

Principal Display Panel

uqora

Founded by a UTI Sufferer

Get Relief

Get Ahead

Convenience Bundle Pack

UTI Pain Relief Max Strength*

Fast targeted relief for pain, burning & urgency

2 Day Supply

12 tablets

99.5 mg Phenazopyridine Hydrochloride

Packaged for convenience.

Not intended to replace medical care.

*Most powerful dose without an Rx.

&

Flush Urinary Tract Drink Mix

Clinical Strength

D-Mannose per serving

Flushes your urinary tract + immune support*

Pink Lemonade Flavor

2 packets

Dietary Supplement

Net Wt. 0.3OZ(10G

* These statements have not been evaluated by the Food and Drug Administration. This product is not intended to diagnose, treat, cure, or prevent any disease.